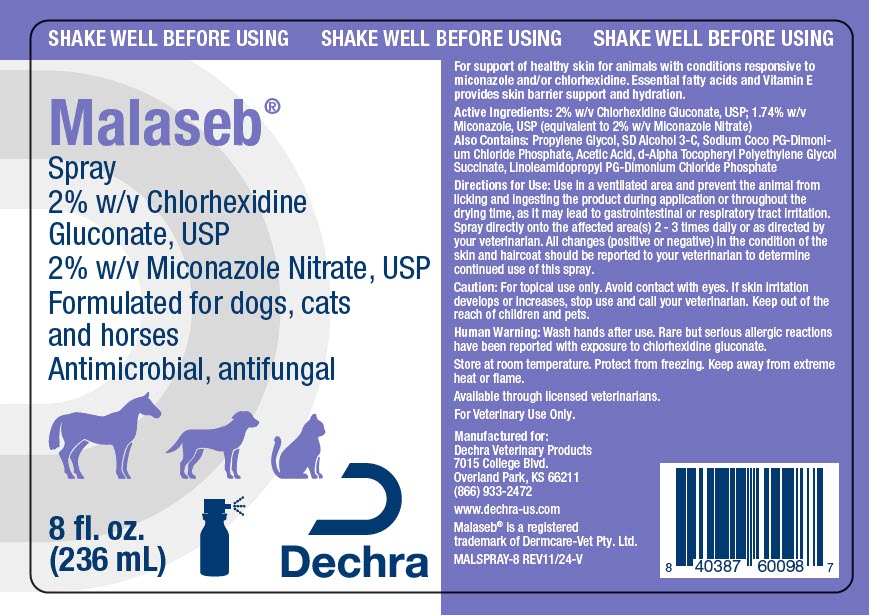 DRUG LABEL: Malaseb
NDC: 17033-186 | Form: SPRAY
Manufacturer: Dechra Veterinary Products
Category: animal | Type: OTC ANIMAL DRUG LABEL
Date: 20241212

ACTIVE INGREDIENTS: CHLORHEXIDINE GLUCONATE 20 mg/1 mL; Miconazole Nitrate 20 mg/1 mL

Malaseb® Spray

VETERINARY INDICATIONS

For support of healthy skin for animals with conditions responsive to miconazole and/or chlorhexidine. Essential fatty acids and Vitamin E provides skin barrier support and hydration.

DESCRIPTION

Active Ingredients: 2% w/v Chlorhexidine Gluconate, USP; 1.74% w/v Miconazole, USP (equivalent to 2% w/v Miconazole Nitrate)

Also Contains: Propylene Glycol, SD Alcohol 3-C, Sodium Coco PG-Dimonium Chloride Phosphate, Acetic Acid, d-Alpha Tocopheryl Polyethylene Glycol Succinate, Linoleamidopropyl PG-Dimonium Chloride Phosphate

DOSAGE AND ADMINISTRATION

Directions for Use: Use in a ventilated area and prevent the animal from licking and ingesting the product during application or throughout the drying time, as it may lead to gastrointestinal or respiratory tract irritation.

Spray directly onto the affected area(s) 2 - 3 times daily or as directed by your veterinarian. All changes (positive or negative) in the condition of the skin and haircoat should be reported to your veterinarian to determine continued use of this spray.

PRECAUTIONS

Caution: For topical use only. Avoid contact with eyes. If skin irritation develops or increases, stop use and call your veterinarian. Keep out of the reach of children and pets.

SAFE HANDLING WARNING

Human Warning: Wash hands after use. Rare but serious allergic reactions have been reported with exposure to chlorhexidine gluconate.

STORAGE AND HANDLING

Store at room temperature. Protect from freezing. Keep away from extreme heat or flame.

Available through licensed veterinarians.

For Veterinary Use Only.

Manufactured for:
Dechra Veterinary Products
7015 College Blvd.
Overland Park, KS 66211
(866) 933-2472
www.dechra-us.com
Malaseb® is a registered
trademark of Dermcare-Vet Pty. Ltd.
MALSPRAY-8 REV11/24-V

PRINCIPAL DISPLAY PANEL - 236 mL Bottle Label

SHAKE WELL BEFORE USING

Malaseb®
Spray
2% w/v Chlorhexidine
Gluconate, USP
2% w/v Miconazole Nitrate, USP
Formulated for dogs, cats
and horses
Antimicrobial, antifungal

8 fl. oz.
(236 mL)

Dechra